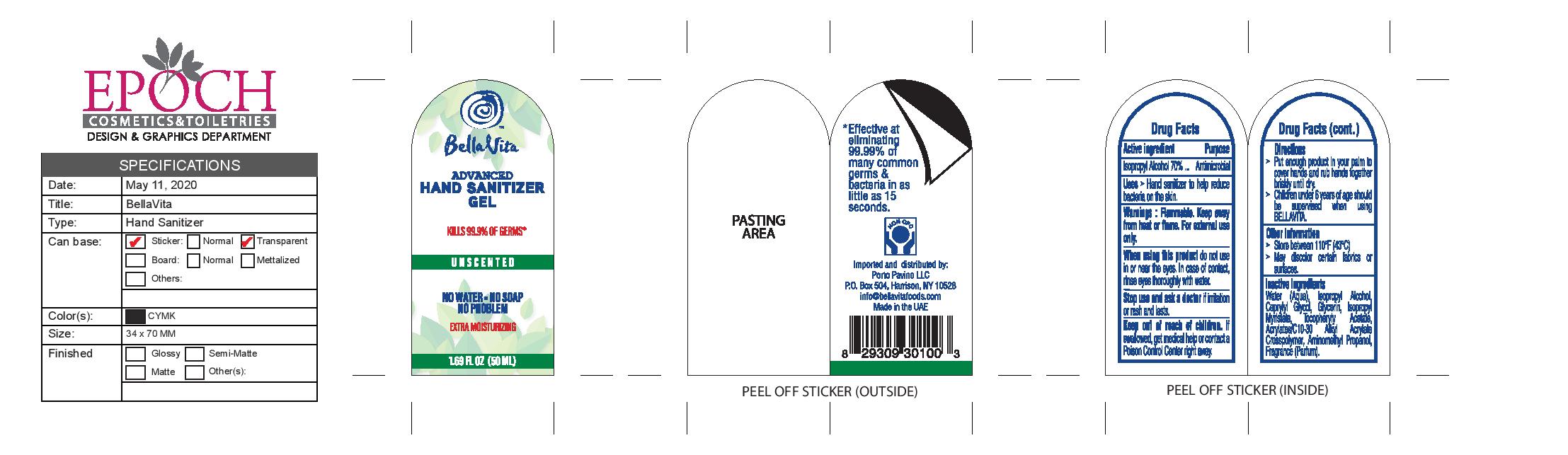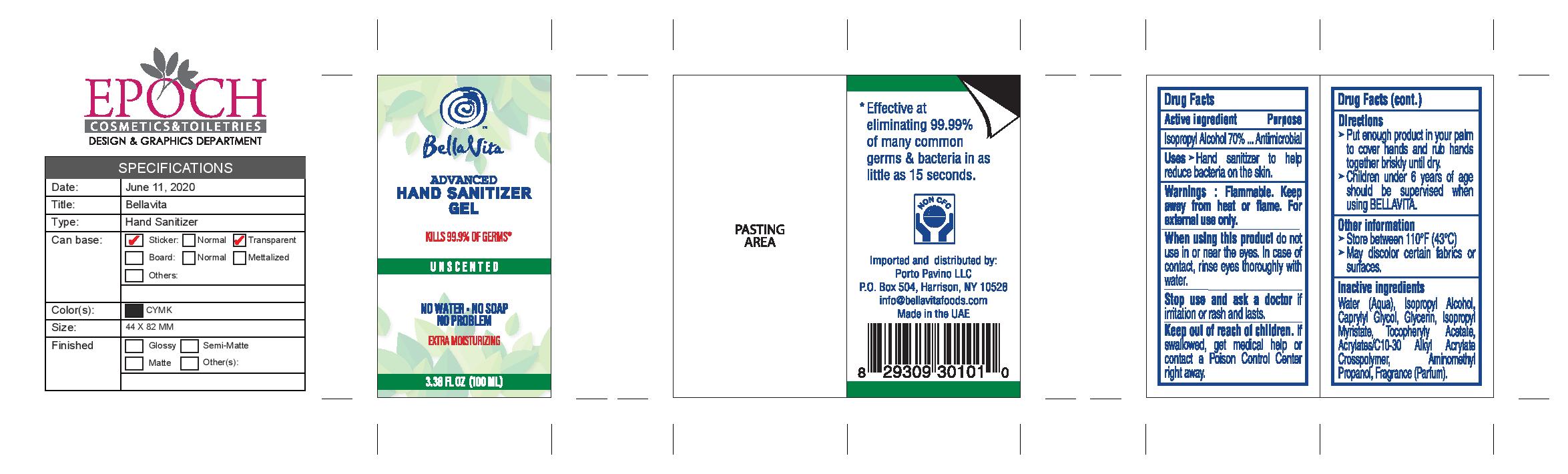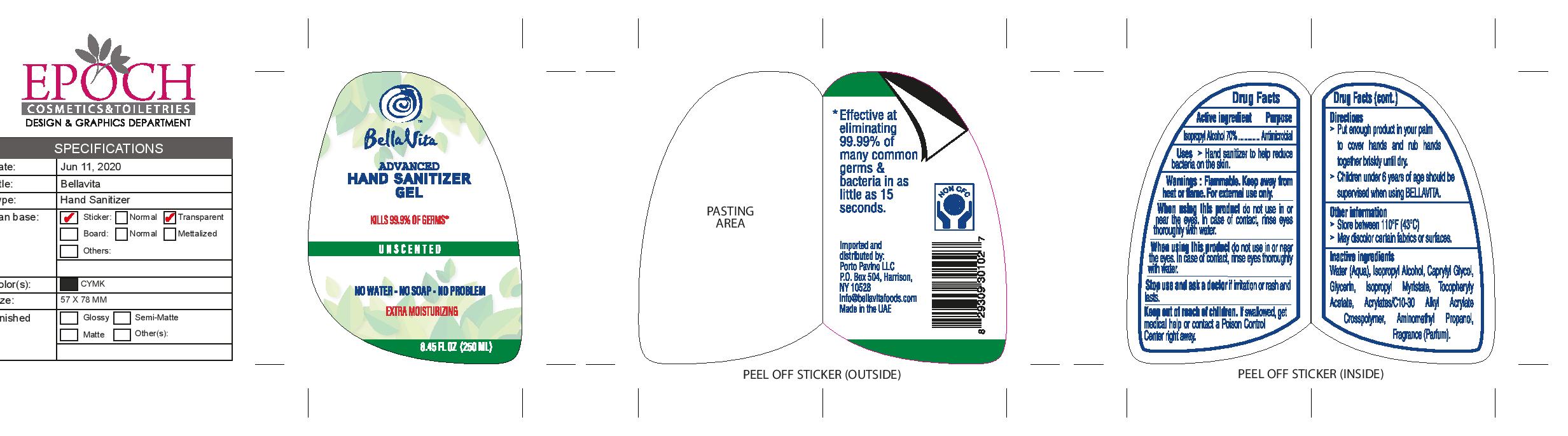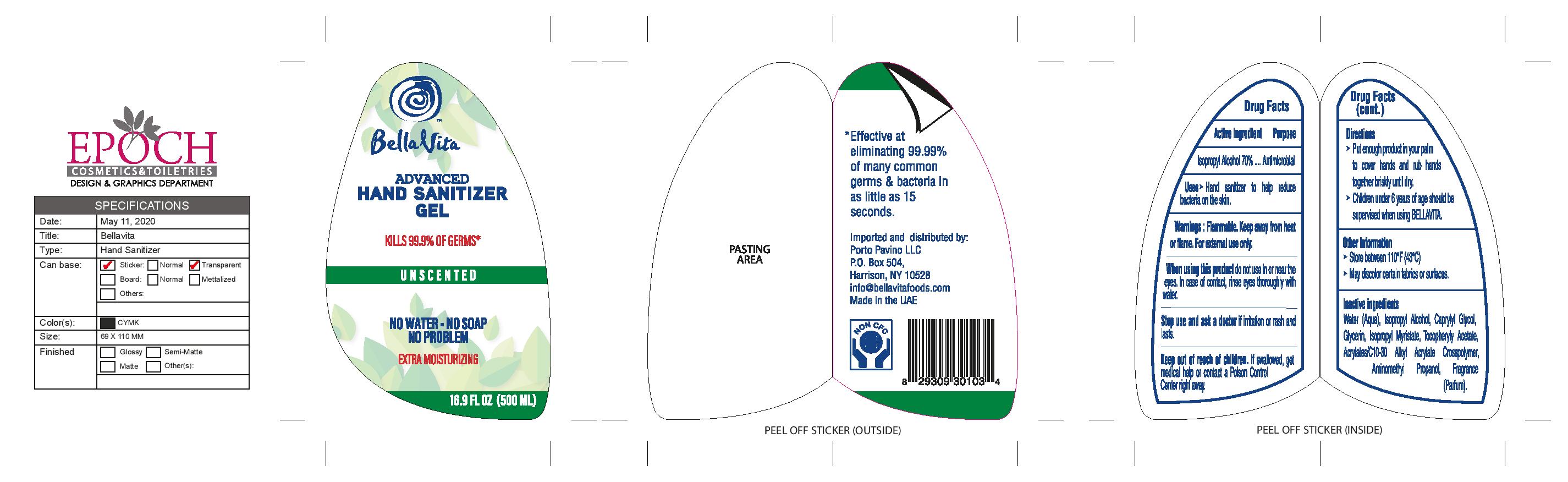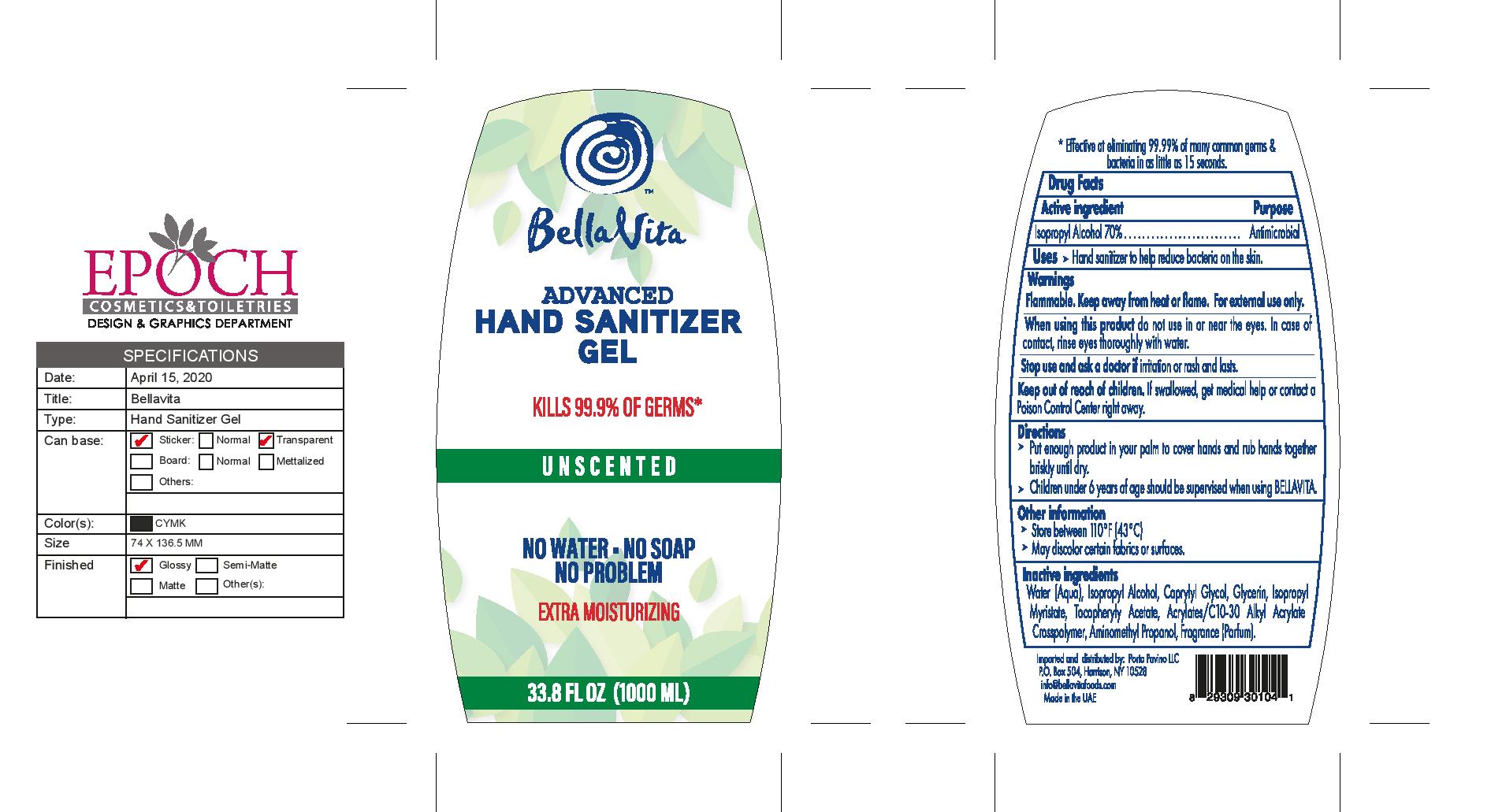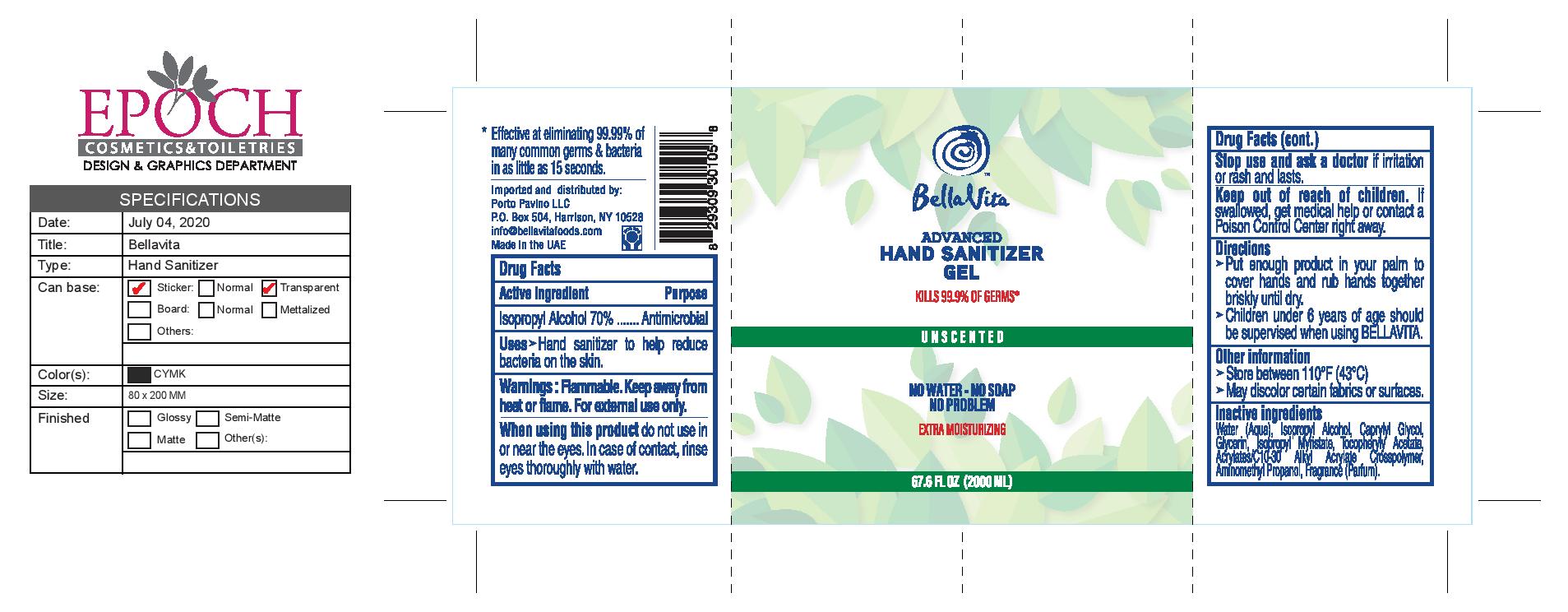 DRUG LABEL: Bella Vita Advanced Hand Sanitizer
NDC: 80309-005 | Form: GEL
Manufacturer: EPOCH Cosmetics and Toiletries Industries LLC
Category: otc | Type: HUMAN OTC DRUG LABEL
Date: 20200902

ACTIVE INGREDIENTS: ISOPROPYL ALCOHOL 70 mL/100 mL
INACTIVE INGREDIENTS: GLYCERIN 1.45 mL/100 mL; HYDROGEN PEROXIDE; WATER; ISOPROPYL MYRISTATE; CARBOMER COPOLYMER TYPE A (ALLYL PENTAERYTHRITOL CROSSLINKED); AMINOMETHYLPROPANOL

Active Ingredient(s)

Isopropyl Alcohol 70%

Purpose

Antimicrobial

Use

Hand Sanitizer to help reduce bacteria on the skin

Warnings

For external use only. Flammable. Keep away from heat or flame

When using this product do not use in or near the eyes. In case of contact with eyes, rinse eyes thoroughly with water.

Stop use and ask a doctor if irritation or rash and lasts.

Keep out of reach of children. If swallowed, get medical help or contact a Poison Control Center right away.

Directions

- Put enough product in your palm to cover hands and rub hands together briskly until dry
- Children under 6 years of age be supervised when using ELEGANT.

Other information

- Store between 110F (43C)
- May discolor certain fabrics

Inactive ingredients

Water (Aqua), Isopropyl Alchohol, Glycol, Glycerin, Isopropyl Myristate, Tocopheryl Acetate, Acrylates/ C10-30 Alkyl Acrylate Corssploymer, Aminomethyl Propanol, Fragrance (Parfum).